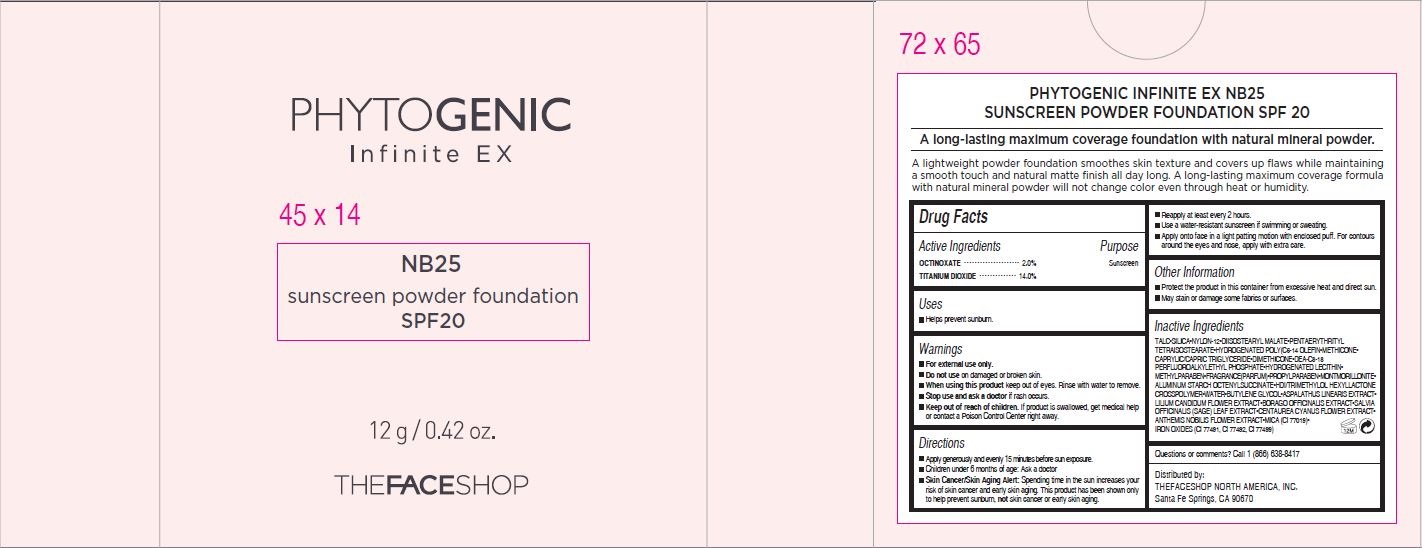 DRUG LABEL: PHYTOGENIC INFINTE EX
NDC: 51523-453 | Form: POWDER
Manufacturer: THEFACESHOP CO., LTD.
Category: otc | Type: HUMAN OTC DRUG LABEL
Date: 20141120

ACTIVE INGREDIENTS: Octinoxate .24 g/12 g; Titanium Dioxide 1.68 g/12 g
INACTIVE INGREDIENTS: MICA

Active Ingredients

Octinoxate 2.0 %

Titanium Dioxide 14.0 %,

Purpose

Sunscreen

Sunscreen

Warnings

For external use only.

Do not use on damaged or broken skin

When using this product keep out of eyes. Rinse with water to remove.

Stop use and ask a doctor if rash occurs.

Keep out of reach of children. If product is swallowed, get medical help or contact a Poison Control Center right away.

Directions

Apply generously and
evenly 15 minutes before sun exposure.
•Children under 6 months of age: Ask a doctor
•Skin Cancer/Skin Aging Alert: Spending time in the sun increases
your risk of skin cancer and early skin aging. This product has been
shown only to help prevent sunburn, not skin cancer or early skin aging.
•Reapply at least every 2 hours.
•Use a water-resistant sunscreen if swimming or sweating.
•Apply onto face in a light patting motion with enclosed puff. For contours
around the eyes and nose, apply with extra care.

Other Information

Protect the product in this container from excessive heat and direct sun

May stain or damage some fabrics or surfaces

Inactive Ingredients

TALC•SILICA•NYLON-12•DIISOSTEARYL MALATE•PENTAERYTHRITYL
TETRAISOSTEARATE•HYDROGENATED POLY(C6-14 OLEFIN•METHICONE•
CAPRYLIC/CAPRIC TRIGLYCERIDE•DIMETHICONE•DEA-C8-18
PERFLUOROALKYLETHYL PHOSPHATE•HYDROGENATED LECITHIN•
METHYLPARABEN•FRAGRANCE(PARFUM)•PROPYLPARABEN•MONTMORILLONITE•
ALUMINUM STARCH OCTENYLSUCCINATE•HDI/TRIMETHYLOL HEXYLLACTONE
CROSSPOLYMER•WATER•BUTYLENE GLYCOL•ASPALATHUS LINEARIS EXTRACT•
LILIUM CANDIDUM FLOWER EXTRACT•BORAGO OFFICINALIS EXTRACT•SALVIA
OFFICINALIS (SAGE) LEAF EXTRACT•CENTAUREA CYANUS FLOWER EXTRACT•
ANTHEMIS NOBILIS FLOWER EXTRACT•MICA (CI 77019)•
IRON OXIDES (CI 77491, CI 77492, CI 77499)

Questions or comments? Call 1 (866) 638-8417

Distributed by:

THEFACESHOP NORTH AMERICA, INC.
Santa Fe Springs, CA 90670

PACKAGE LABEL

PHYTOGENIC

Infinite EX

NB25

sunscreen powder foundation

SPF20